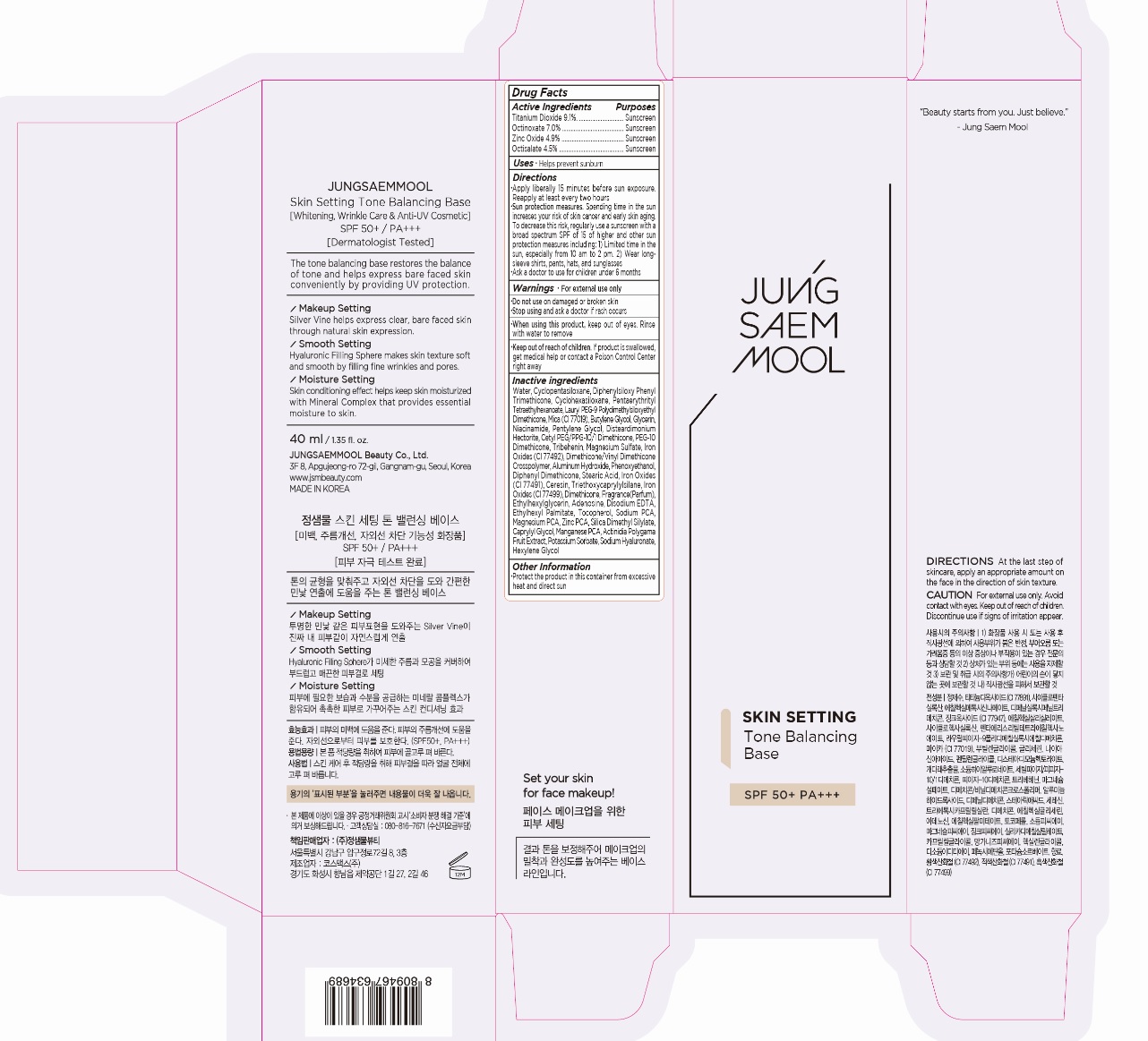 DRUG LABEL: JUNGSAEMMOOL Skin Setting Tone Balancing Base
NDC: 71261-010 | Form: CREAM
Manufacturer: Jungsaemmool Beauty Co., Ltd.
Category: otc | Type: HUMAN OTC DRUG LABEL
Date: 20200714

ACTIVE INGREDIENTS: TITANIUM DIOXIDE 91 mg/1 mL; OCTINOXATE 70 mg/1 mL; ZINC OXIDE 49 mg/1 mL; OCTISALATE 45 mg/1 mL
INACTIVE INGREDIENTS: WATER; CYCLOMETHICONE 5; DIPHENYLSILOXY PHENYL TRIMETHICONE; CYCLOMETHICONE 6; PENTAERYTHRITYL TETRAETHYLHEXANOATE; LAURYL PEG-9 POLYDIMETHYLSILOXYETHYL DIMETHICONE; MICA; BUTYLENE GLYCOL; GLYCERIN; NIACINAMIDE; PENTYLENE GLYCOL; DISTEARDIMONIUM HECTORITE; CETYL PEG/PPG-10/1 DIMETHICONE (HLB 2); PEG-10 DIMETHICONE (600 CST); TRIBEHENIN; MAGNESIUM SULFATE, UNSPECIFIED FORM; FERRIC OXIDE YELLOW; DIMETHICONE/VINYL DIMETHICONE CROSSPOLYMER (HARD PARTICLE); ALUMINUM HYDROXIDE; PHENOXYETHANOL; DIPHENYL DIMETHICONE (100 CST); STEARIC ACID; FERRIC OXIDE RED; CERESIN; TRIETHOXYCAPRYLYLSILANE; FERROSOFERRIC OXIDE; DIMETHICONE; ETHYLHEXYLGLYCERIN; ADENOSINE; EDETATE DISODIUM ANHYDROUS; ETHYLHEXYL PALMITATE; TOCOPHEROL; SODIUM PYRROLIDONE CARBOXYLATE; MAGNESIUM PIDOLATE; ZINC PIDOLATE; SILICA DIMETHYL SILYLATE; CAPRYLYL GLYCOL; MANGANESE PIDOLATE; ACTINIDIA POLYGAMA FRUIT; POTASSIUM SORBATE; HYALURONATE SODIUM; HEXYLENE GLYCOL

71261-010_JUNGSAEMMOOL Skin Setting Tone Balancing Base

ACTIVE INGREDIENT

Titanium Dioxide 9.1%
Octinoxate 7.0%
Zinc Oxide 4.9%
Octisalate 4.5%

PURPOSE

Sunscreen

INDICATIONS AND USAGE

Helps prevent sunburn

DOSAGE AND ADMINISTRATION

Apply liberally 15 minutes before sun exposure. Reapply at least every two hours

Sun protection measures. Spending time in the sun increases your risk of skin cancer and early skin aging. To decrease this risk, regularly use a sunscreen with a broad spectrum SPF of 15 of higher and other sun protection measures including: 1) Limited time in the sun, especially from 10 am to 2 pm. 2) Wear long-sleeve shirts, pants, hats, and sunglasses

Ask a doctor to use for children under 6 months

WARNINGS

For external use only

Do not use on damaged or broken skin

When using this product, keep out of eyes. Rinse with water to remove.

Stop using and ask a doctor if rash occurs.

KEEP OUT OF REACH OF CHILDREN

Keep out of reach of the children. If product is swallowed, get medical help or contact a poison control center right away.

INACTIVE INGREDIENT

Water, Cyclopentasiloxane, Diphenylsiloxy Phenyl Trimethicone, Cyclohexasiloxane, Pentaerythrityl Tetraethylhexanoate, Lauryl PEG-9 Polydimethylsiloxyethyl Dimethicone, Mica (CI 77019), Butylene Glycol, Glycerin, Niacinamide, Pentylene Glycol, Disteardimonium Hectorite, Cetyl PEG/PPG-10/1 Dimethicone, PEG-10 Dimethicone, Tribehenin, Magnesium Sulfate, Iron Oxides (CI 77492), Dimethicone/Vinyl Dimethicone Crosspolymer, Aluminum Hydroxide, Phenoxyethanol, Diphenyl Dimethicone, Stearic Acid, Iron Oxides (CI 77491), Ceresin, Triethoxycaprylylsilane, Iron Oxides (CI 77499), Dimethicone, Fragrance(Parfum), Ethylhexylglycerin, Adenosine, Disodium EDTA, Ethylhexyl Palmitate, Tocopherol, Sodium PCA, Magnesium PCA, Zinc PCA, Silica Dimethyl Silylate, Caprylyl Glycol, Manganese PCA, Actinidia Polygama Fruit Extract, Potassium Sorbate, Sodium Hyaluronate, Hexylene Glycol

OTHER SAFETY INFORMATION

Protect the product in the container from excessive heat and direct sun